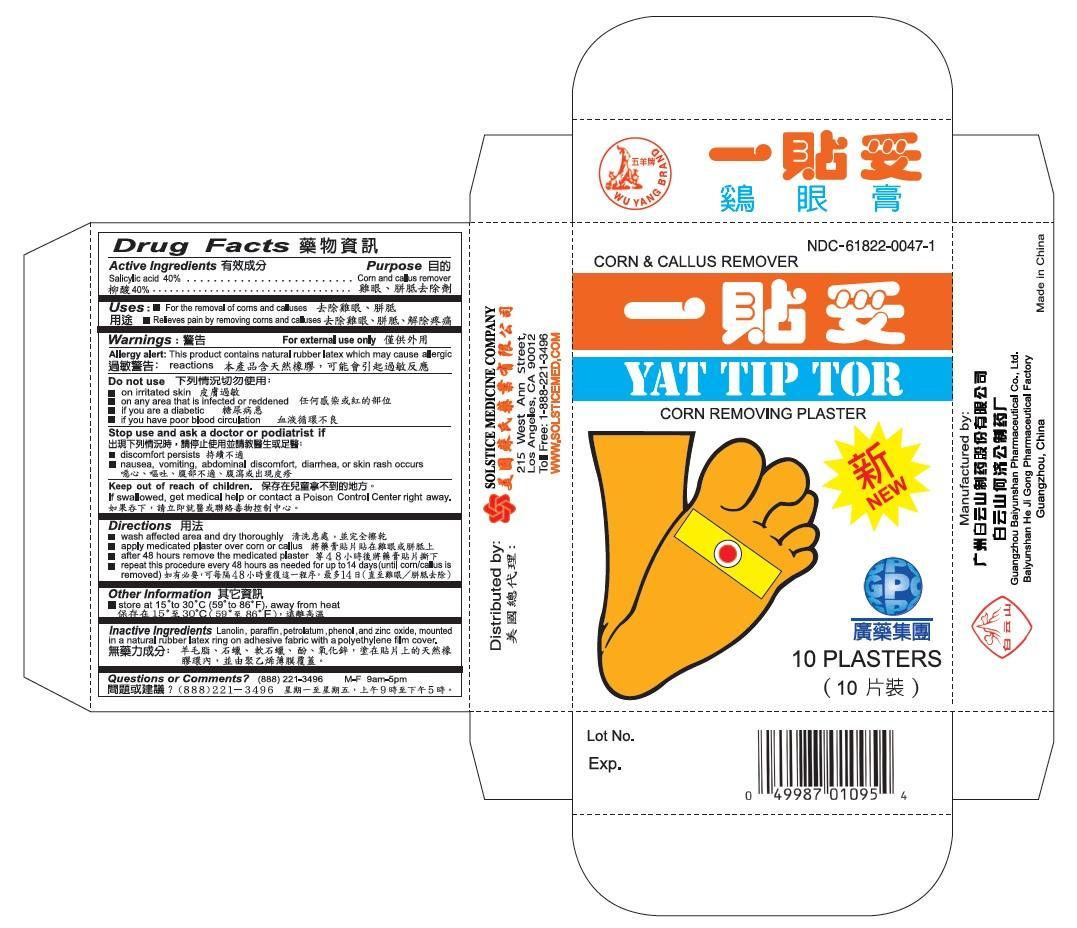 DRUG LABEL: YAT TIP TOR
NDC: 61822-0047 | Form: PLASTER
Manufacturer: GUANGZHOU BAIYUNSHAN PHARMACEUTICAL CO., LTD. BAIYUNSHAN HEJIGONG PHARMACEUTICAL FACTORY
Category: otc | Type: HUMAN OTC DRUG LABEL
Date: 20191113

ACTIVE INGREDIENTS: SALICYLIC ACID 40 g/1 1
INACTIVE INGREDIENTS: LANOLIN; PARAFFIN; PETROLATUM; PHENOL; ZINC OXIDE

Drug Facts

Active Ingredient
Salicylic acid 40%

Purpose
Corn and callus remover

Uses
For the removal of corns and calluses
Relieves pain by removing corns and calluses

Warnings
For external use only
Allergy alert: This product contains natural rubber latex which may cause allergic reactions

Do not use
on irritated skin
on any area that is infected or reddened
if you are a diabetic
if you have poor blood circulation

Stop use and ask a doctor or podiatrist if
discomfort persists
nausea, vomiting, abdominal discomfort, diarrhea, or skin rash occurs

Keep out of reach of children.
If swallowed, get medical help or contact an Poison Control Center right away.

Directions
wash affected area and dry thoroughly
apply medicated plaster over corn or callus
after 48 hours remove the medicated plaster
repeat this procedure every 48 hours as needed for up to 14 days (until corn/callus is removed)

Other Information
store at 15° to 30° C (59° to 86° F), away from heat

Inactive Ingredients
Lanolin, paraffin, petrolatum, phenol, and zinc oxide, mounted in a natural rubber latex ring on adhesive fabric with a polyethylene film cover.

Questions or Comments? (888) 221-3496 M-F 9am to 5p

PACKAGE LABEL

Yat Tip Tor

Corn & Callus Remover

NDC 61822-0047-1

10 Plasters